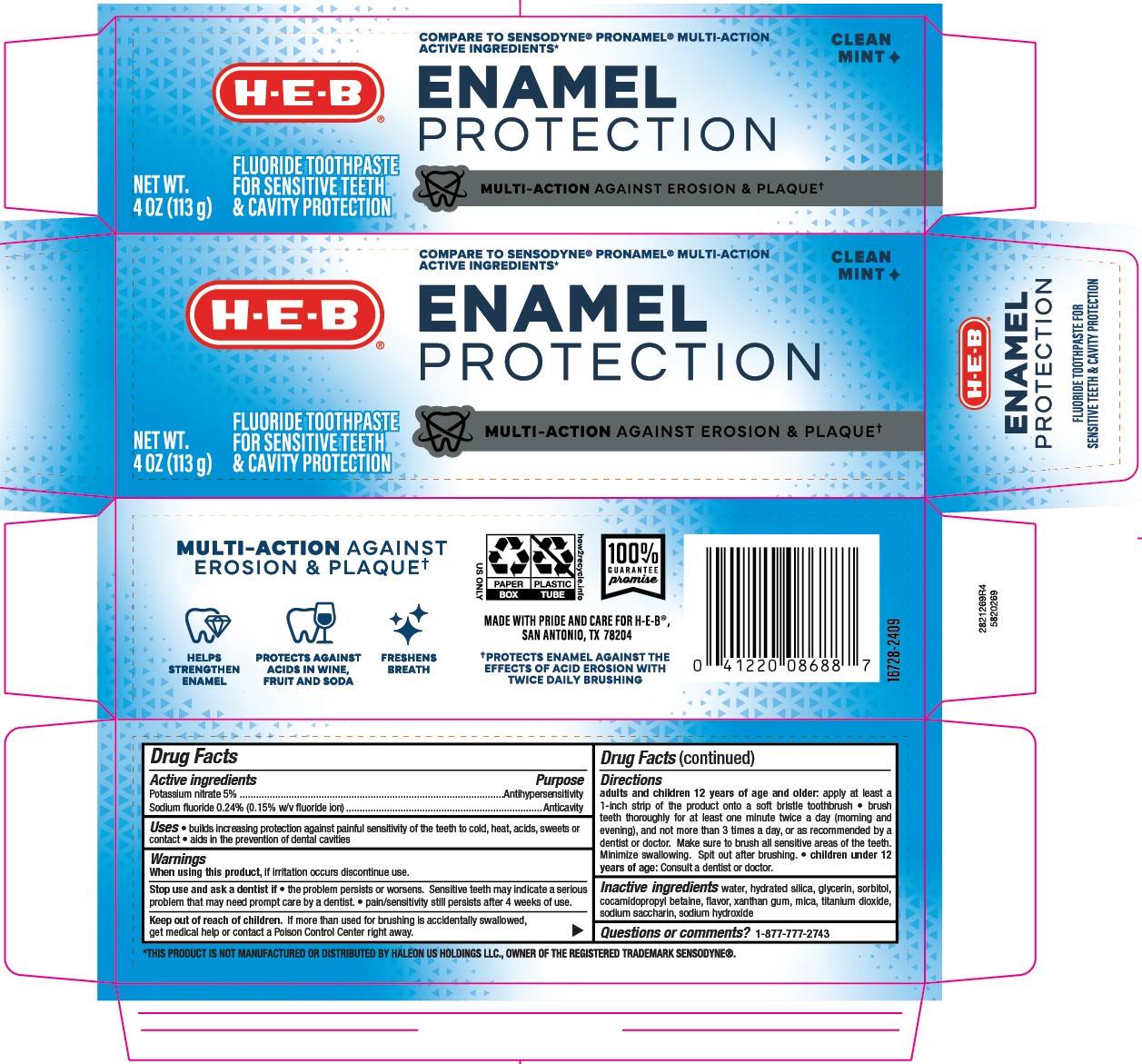 DRUG LABEL: HEB Enamel Protection
NDC: 37808-336 | Form: PASTE, DENTIFRICE
Manufacturer: HEB
Category: otc | Type: HUMAN OTC DRUG LABEL
Date: 20251121

ACTIVE INGREDIENTS: SODIUM FLUORIDE 0.15 g/100 g; POTASSIUM NITRATE 5 g/100 g
INACTIVE INGREDIENTS: SACCHARIN SODIUM; WATER; SORBITOL; TITANIUM DIOXIDE; SODIUM HYDROXIDE; GLYCERIN; XANTHAN GUM; HYDRATED SILICA; COCAMIDOPROPYL BETAINE; MICA

5820269 HEB Enamel Protection Multi-Action Sensitive Toothpaste

Drug Facts

Active ingredients

Potassium nitrate 5%

Sodium fluoride 0.24% (0.15% w/v fluoride ion)

Purpose

Antihypersensitivity

Anticavity

Uses

- builds increasing protection against painful sensitivity of the teeth
- aids in the prevention of dental cavities

When using this product, if irritation occurs discontinue use.

Stop use and see your dentist if the problem persists or worsens. Sensitive teeth may indicate a serious problem that may need prompt care by a dentist.

- pain/sensitivity still persists after 4 weeks of use

Keep out of reach of children. If more than used for brushing is accidentally swallowed, get medical help or contact a Poison Control Center right away.

Directions

Adults and children 12 years of age and older: Apply at least a 1-inch strip of the product onto a soft bristle toothbrush.

- Brush teeth thoroughly for at least one minute, preferably after each meal or at least twice a day (morning and evening) or as recommended by a dentist or physican
- Make sure to brush all sensitive areas of the teeth
- Minimize swallowing.
- Spit out after brushing.

Children under 12 years of age: Consult a dentist or a doctor.

INACTIVE INGREDIENT

Inactive ingredients water, hydrated silica, glycerin, sorbitol, cocamidopropyl betaine, flavor, xanthan gum, mica, titanium dioxide, sodium saccharin, sodium hydroxide

STORAGE AND HANDLING

Store in a cool dry place. Keep tube capped when not in use.

Questions or Comments? CALL 1-877-777-2743

MADE WITH PRIDE AND CARE FOR H-E-B®

SAN ANTONIO, TX 78204